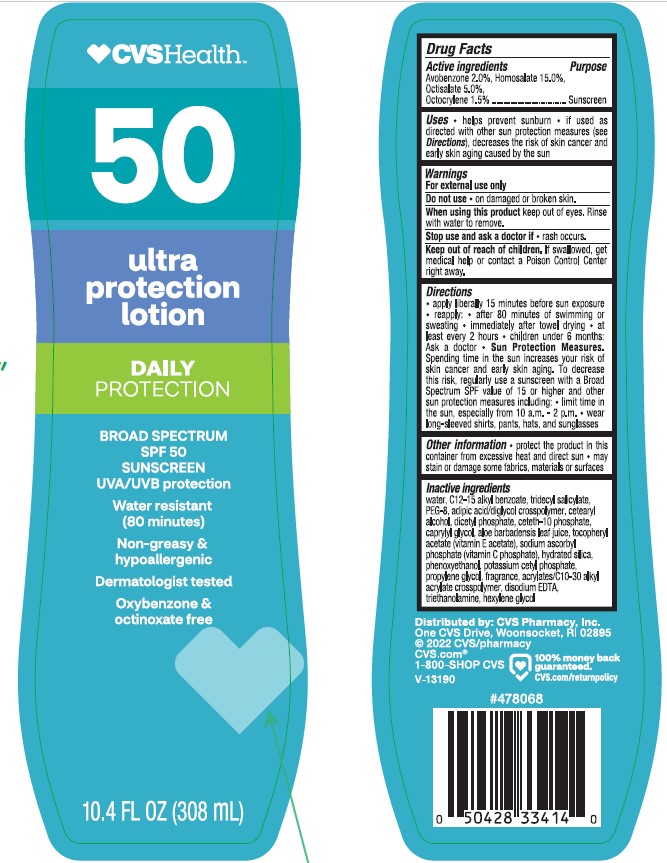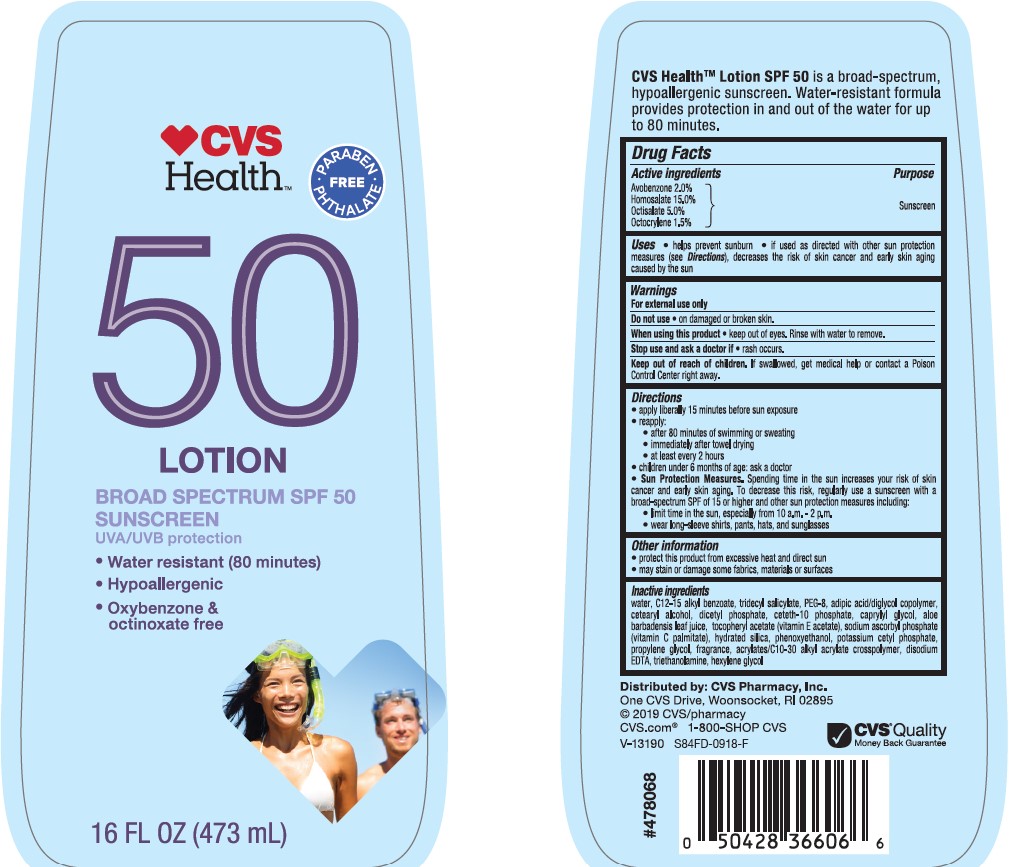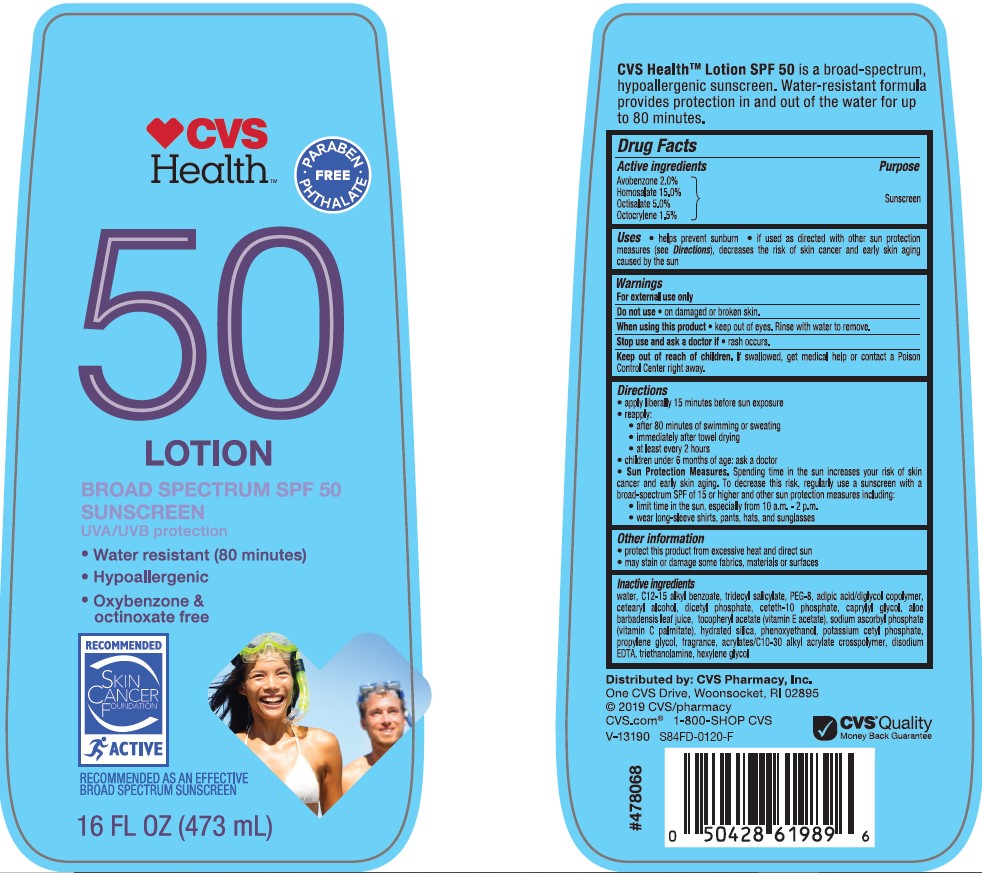 DRUG LABEL: CVS Health SPF 50
NDC: 51316-010 | Form: LOTION
Manufacturer: CVS Pharmacy
Category: otc | Type: HUMAN OTC DRUG LABEL
Date: 20241017

ACTIVE INGREDIENTS: OCTISALATE 50 mg/1 mL; AVOBENZONE 20 mg/1 mL; HOMOSALATE 150 mg/1 mL; OCTOCRYLENE 15 mg/1 mL
INACTIVE INGREDIENTS: CAPRYLYL GLYCOL; CARBOMER COPOLYMER TYPE A (ALLYL PENTAERYTHRITOL CROSSLINKED); WATER; ADIPIC ACID/DIGLYCOL CROSSPOLYMER (20000 MPA.S); POTASSIUM CETYL PHOSPHATE; CARBOMER INTERPOLYMER TYPE B (ALLYL PENTAERYTHRITOL CROSSLINKED); POLYETHYLENE GLYCOL 400; ALKYL (C12-15) BENZOATE; CETOSTEARYL ALCOHOL; PHENOXYETHANOL; ALOE VERA LEAF; SODIUM ASCORBYL PHOSPHATE; EDETATE DISODIUM; .ALPHA.-TOCOPHEROL ACETATE; PROPYLENE GLYCOL; TROLAMINE; SILICON DIOXIDE; DIHEXADECYL PHOSPHATE; CETETH-10 PHOSPHATE; TRIDECYL SALICYLATE; HEXYLENE GLYCOL

CVS Health SPF 50 Lotion

Active ingredients

Avobenzone 2.0%, Homosalate 15.0%, Octisalate 5.0%, Octocrylene 1.5%

Purpose

Sunscreen

Uses

- helps prevent sunburn
- if used as directed with other sun protection measures (see Directions), decreases the risk of skin cancer and early skin aging caused by the sun

Warnings

For external use only

Do not use

- on damaged or broken skin.

When using this product

keep out of eyes. Rinse with water to remove.

Stop use and ask doctor if

- rash occurs.

Keep out of reach of children.

If product is swallowed, get medical help or contact a Poison Control Center right away.

Directions

• apply liberally 15 minutes before sun exposure
• reapply:
• after 80 minutes of swimming or sweating
• immediately after towel drying
• at least every 2 hours
• Sun Protection Measures. Spending time in the sun increases your risk of skin cancer and early skin aging. To decrease this risk, regularly use a sunscreen with a Broad Spectrum SPF value of 15 or higher and other sun protection measures including:
• limit time in the sun, especially from 10 a.m. - 2 p.m.
• wear long-sleeved shirts, pants, hats, and sunglasses
• children under 6 months: Ask a doctor

Inactive ingredients

water, C12-15 alkyl benzoate, tridecyl salicylate, PEG-8, adipic acid/diglycol crosspolymer, cetearyl alcohol, dicetyl phosphate, ceteth-10 phosphate, caprylyl glycol, aloe barbadensis leaf juice, tocopheryl acetate (vitamin E acetate), sodium ascorbyl phosphate (vitamin C phosphate), hydrated silica, phenoxyethanol, potasium cetyl phosphate, propylene glycol, fragrance, acrylates/C10-30 alkyl acrylate crosspolymer, disodium EDTA, triethanolamine, hexylene glycol

Other information

• protect the product in this container from excessive heat and direct sun
• may stain or damage some fabrics, materials or surfaces